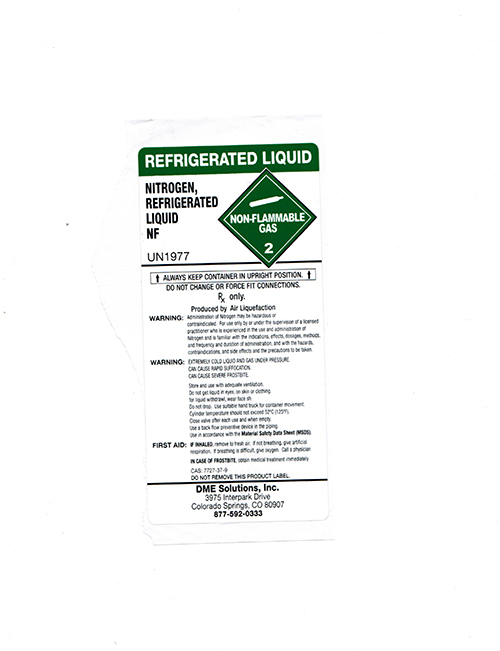 DRUG LABEL: Nitrogen
NDC: 68769-005 | Form: GAS
Manufacturer: Colorado Compressed Gases
Category: prescription | Type: HUMAN PRESCRIPTION DRUG LABEL
Date: 20231128

ACTIVE INGREDIENTS: NITROGEN 99 L/100 L

Nitrogen

Principal for Nitrogen Product

REFRIGERATED LIQUID

NITROGEN, REFRIGERATED
LIQUID NF
UN1977

ALWAYS KEEP CONTAINER IN UPRIGHT POSITION
DO NOT CHANGE OR FORCE FIT CONNECTIONS.

RX only.

Produced by Air Liquefication

WARNING: Administration of Nitrogen may be hazardous or
contraindicated. For use only by or under the supervision of a licensed
practitioner who is experienced in the use and administration of
Nitrogen and is familiar with the indications, effects, dosages, methods,
and frequency and duration of administration, and with the hazards,
contraindications, and side effects and the precations to be taken.
WARNING: EXTREMELY COLD LIQUID AND GAS UNDER PRESSURE.

CAN CAUSE RAPID SUFFOCATION.

CAN CAUSE SEVERE FROSTBITE.

Store and use with adequate ventilation.

Do not get liquid in eyes, on skin or clothing.

fo liiquid withdrawl, wear face shield

Do not drop. Use suitable hand truck for container movement.

Cylinder temperature should not exceed 52 C (125 F)

Close valve after each use and when empty.

Use a back flow preventive device tin the piping.

Use in accordance with the Material Safety Data Sheet (MSDS)

FIRST AID: IF INHALED, remove to fresh air. If not breathing, give artificial
respiration. If breathing is difficult, give oxygen. Call a physician.

IN CASE OF FROSTBITE, obtain medical treatment immediately

CAS: 7727-37-9
DO NOT REMOVE THIS PRODUCT LABEL.